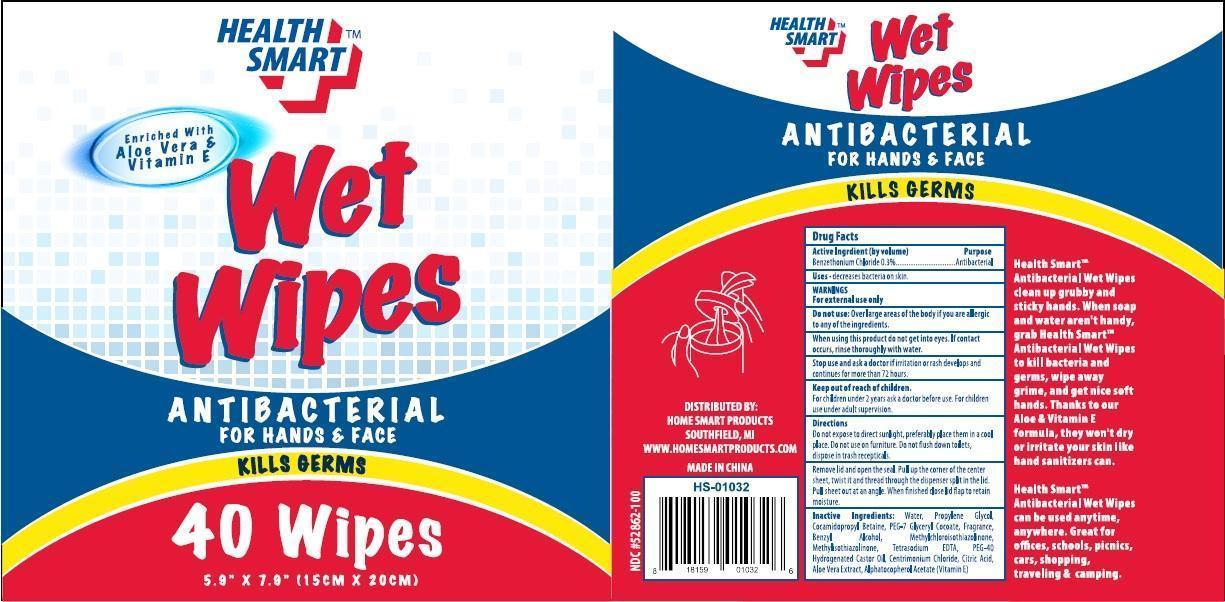 DRUG LABEL: Health Smart Antibacterial Wet Wipes
NDC: 52862-100 | Form: SWAB
Manufacturer: International Wholesale, Inc.
Category: otc | Type: HUMAN OTC DRUG LABEL
Date: 20150705

ACTIVE INGREDIENTS: BENZETHONIUM CHLORIDE 0.3 g/100 1
INACTIVE INGREDIENTS: WATER; PROPYLENE GLYCOL; COCAMIDOPROPYL BETAINE; PEG-7 GLYCERYL COCOATE; BENZYL ALCOHOL; METHYLCHLOROISOTHIAZOLINONE; METHYLISOTHIAZOLINONE; EDETATE SODIUM; PEG-40 CASTOR OIL; CETRIMONIUM CHLORIDE; CITRIC ACID MONOHYDRATE; ALOE VERA LEAF; ALPHA-TOCOPHEROL ACETATE

Drug Facts

Active Ingredient(by volume)

Benzethonium Chloride 0.3%

Purpose

Antibacterial

Uses

•decreases bacteria on skin.

WARNINGS

For external use only.

Do not use:

Over large areas of the body if you are allergic to any of the ingredients.

When using this product do not get into eyes. If contact occurs, rinse thoroughly with water.

Stop use and ask a doctor if irritation or rash develops and continues for more than 72 hours.

Keep out of reach of children

For children under 2 years ask a doctor before use. For children use under adult supervision.

Directions

Do not expose to direct sunlight, preferably place them in a cool place. Do not use on furniture. Do not flush down toilets, dispose in a trash recepticals.

DOSAGE AND ADMINISTRATION

Remove lid and open the seal. Pull up the corner of the center sheet, twist it and thread through the dispenser split in the lid. Pull sheet out at an angle. When finished close the lid flap to retain moisture.

Inactive Ingredients

Water, Propylene Glycol, Cocamidopropyl Betaine, PEG-7 Glyceryl Cocoate, Fragrance, Benzyl Alcohol, Methylchloroisothiazolinone, Methylisothiazolinone, Tetrasodium EDTA, PEG-40 Hydrogenated Castor Oil, Cetrimonium Chloride, Citric Acid, Aloe Vera Extract, Alphatocopherol Acetate (Vitamin E)

Health Smart TM

Antibacterial Wet Wipes clean up grubby and sticky hands. When soap and water aren't handy. grab Health Smart TM Antibacterial Wet Wipes to kill bacteria and germs, wipe away grime, and get nice soft hands. Thanks to our Aloe & Vitamin E formula, they won't dry or irritate your skin like hand sanitizers can.

Health Smart TM
Antibacterial Wet Wipes can be used anytime, anywhere. Great for offices, schools, picnics, cars, shopping, travelling & camping.

DISTRIBUTED BY:
HOME SMART PRODUCTS
PRODUCTS
SOUTHFIELD, MI
WWW.HOMESMARTPRODUCTS.COM
MADE IN CHINA
NDC #52862-100

Package Label

HEALTH
SMARTTM

Enriched With
Aloe Vera &
Vitamin E

Wet
Wipes

ANTIBACTERIAL
FOR HANDS & FACE
KILLS GERMS

40 WIPES

5.9" x 7.9" (15 CM X 20 CM)